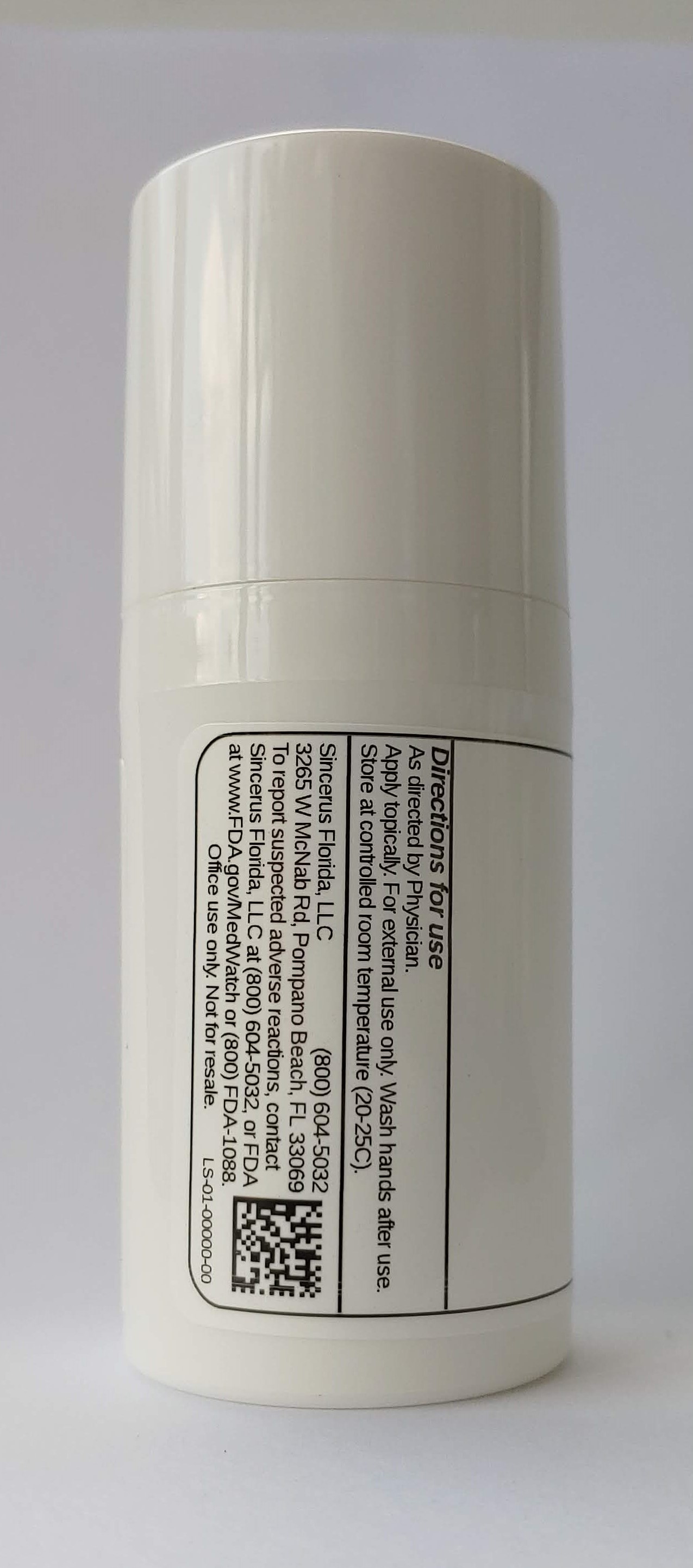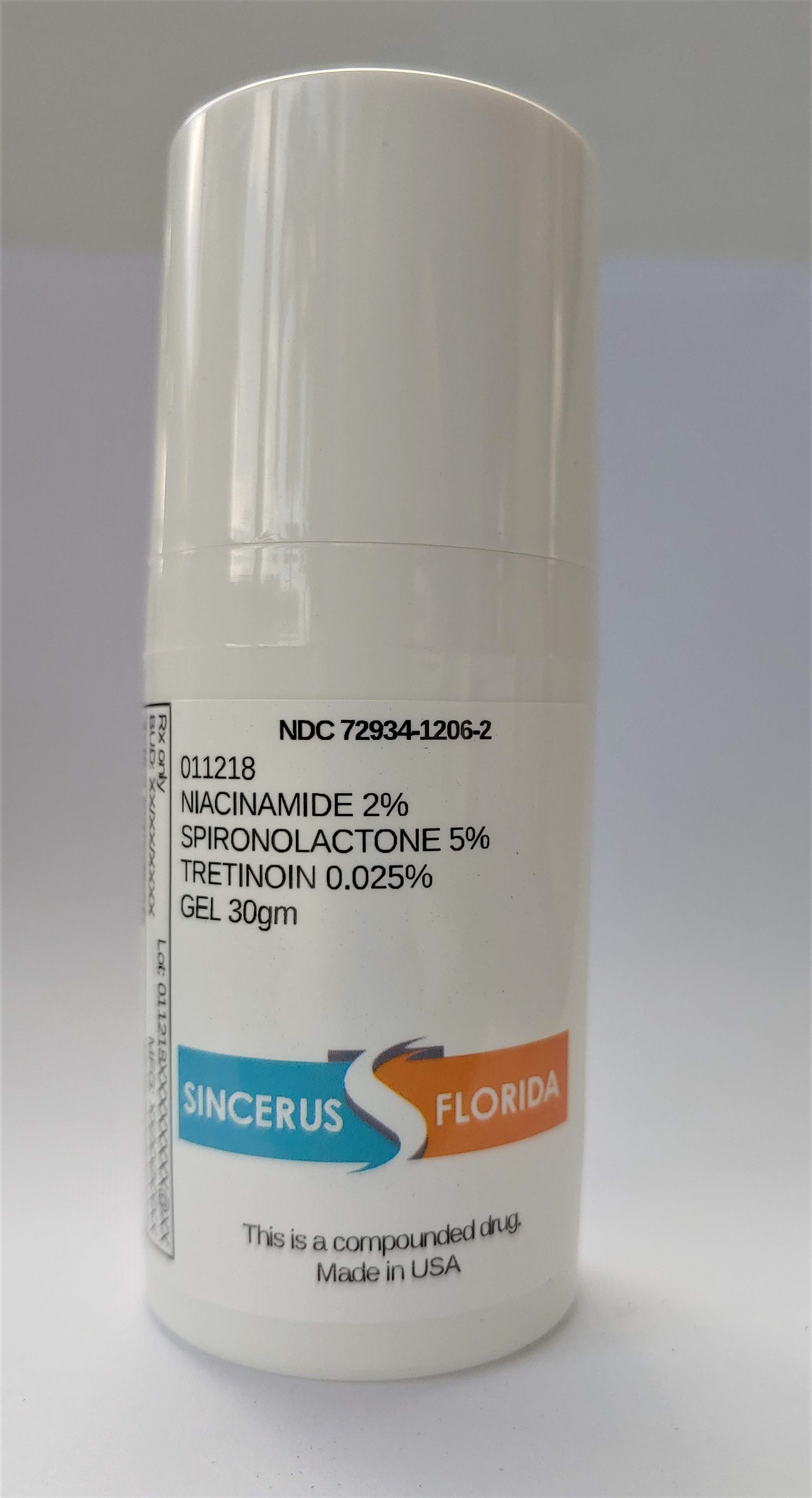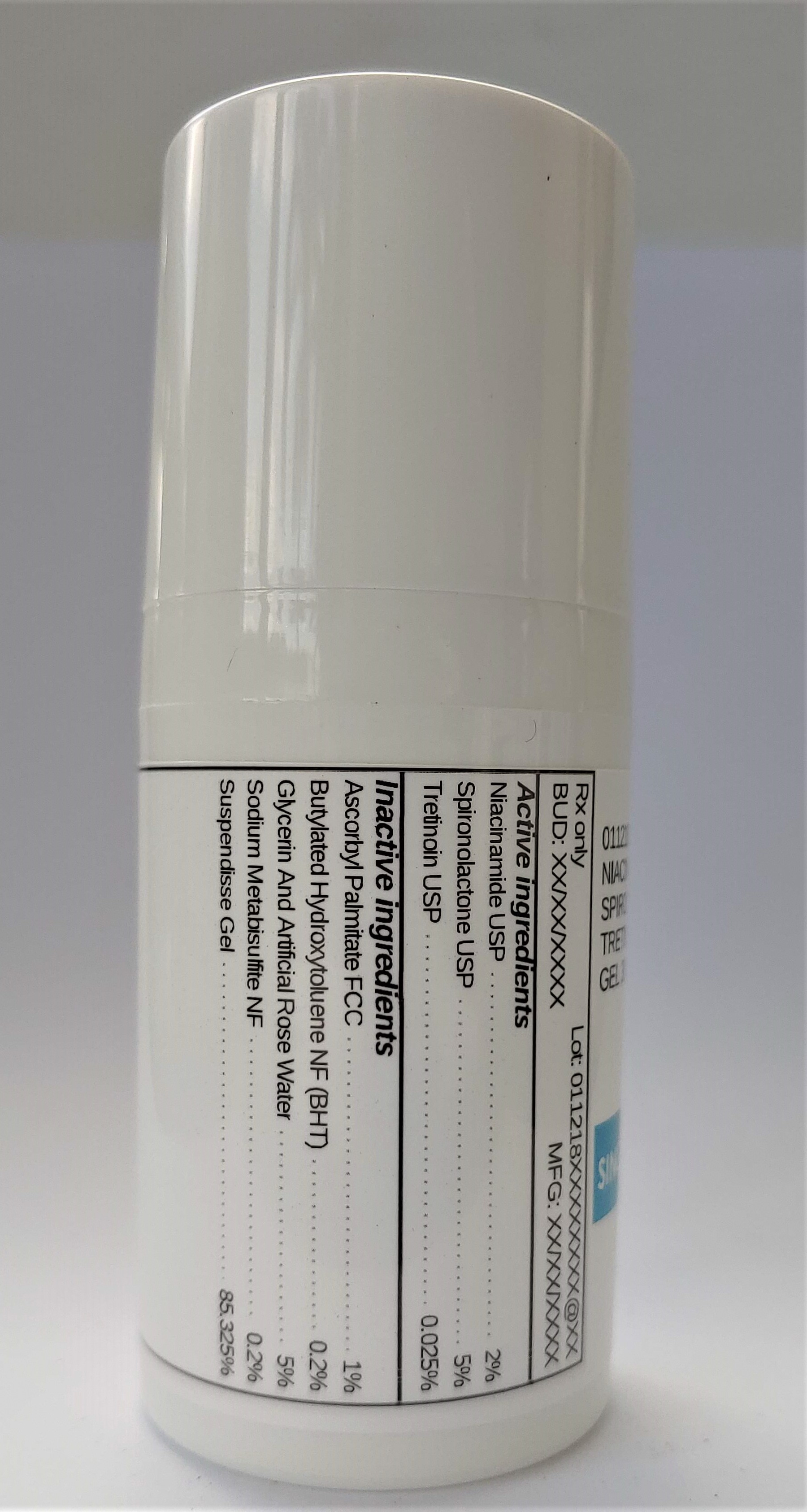 DRUG LABEL: 011218 NIACINAMIDE 2% / SPIRONOLACTONE 5% / TRETINOIN 0.025%
NDC: 72934-1206 | Form: GEL
Manufacturer: Sincerus Florida, LLC
Category: prescription | Type: HUMAN PRESCRIPTION DRUG LABEL
Date: 20200702

ACTIVE INGREDIENTS: NIACINAMIDE 2 g/100 g; SPIRONOLACTONE 5 g/100 g; TRETINOIN 0.025 g/100 g

011218 NIACINAMIDE 2% / SPIRONOLACTONE 5% / TRETINOIN 0.025%